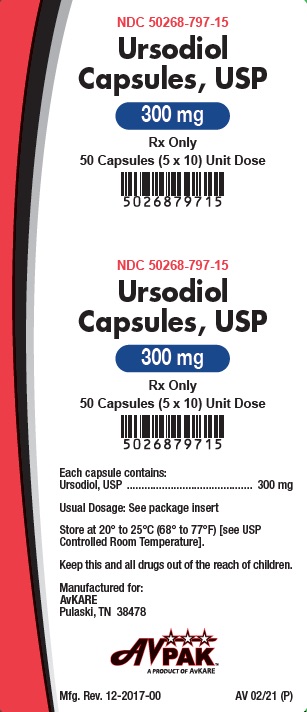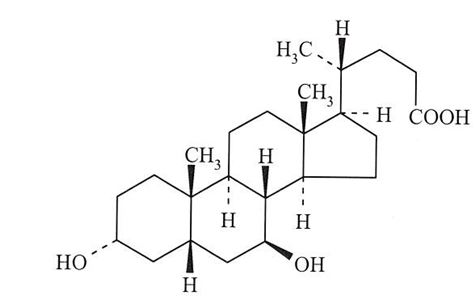 DRUG LABEL: Ursodiol
NDC: 50268-797 | Form: CAPSULE
Manufacturer: AvPAK
Category: prescription | Type: HUMAN PRESCRIPTION DRUG LABEL
Date: 20260112

ACTIVE INGREDIENTS: URSODIOL 300 mg/1 1
INACTIVE INGREDIENTS: ALCOHOL; AMMONIA; BUTYL ALCOHOL; FERRIC OXIDE RED; FERROSOFERRIC OXIDE; GELATIN; ISOPROPYL ALCOHOL; MAGNESIUM STEARATE; POTASSIUM HYDROXIDE; PROPYLENE GLYCOL; SHELLAC; SILICON DIOXIDE; STARCH, CORN; TITANIUM DIOXIDE; WATER

Ursodiol Capsules, USP
Rx Only

Prescribing Information

SPECIAL NOTE

Gallbladder stone dissolution with ursodiol treatment requires months of therapy. Complete dissolution does not occur in all patients and recurrence of stones within 5 years has been observed in up to 50% of patients who do dissolve their stones on bile acid therapy. Patients should be carefully selected for therapy with ursodiol, and alternative therapies should be considered.

DESCRIPTION

Ursodiol is a bile acid available as 300 mg capsules suitable for oral administration.

Ursodiol (ursodeoxycholic acid), is a naturally occurring bile acid found in small quantities in normal human bile and in the biles of certain other mammals. Ursodiol, USP is a white or almost white crystalline powder, practically insoluble in water, freely soluble in ethanol (96%), slightly soluble in acetone and practically insoluble in methylene chloride.

The chemical name for ursodiol is 3α,7β-Dihydroxy-5β-cholan-24-oic acid (C24H40O4). Ursodiol, USP has a molecular weight of 392.6 g/mol. Its structure is shown below:

Inactive Ingredients: Colloidal silicon dioxide, gelatin, iron oxide red, magnesium stearate, starch (biological source: maize), titanium dioxide and water.

Each capsule is imprinted with black pharmaceutical ink which contains butyl alcohol, dehydrated alcohol, ferrosoferric oxide, isopropyl alcohol, purified water, potassium hydroxide, propylene glycol, shellac and strong ammonia solution.

CLINICAL PHARMACOLOGY

About 90% of a therapeutic dose of ursodiol is absorbed in the small bowel after oral administration. After absorption, ursodiol enters the portal vein and undergoes efficient extraction from portal blood by the liver (i.e. there is a large “first-pass” effect) where it is conjugated with either glycine or taurine and is then secreted into the hepatic bile ducts. Ursodiol in bile is concentrated in the gallbladder and expelled into the duodenum in gallbladder bile via the cystic and common ducts by gallbladder contractions provoked by physiologic responses to eating. Only small quantities of ursodiol appear in the systemic circulation and very small amounts are excreted into urine. The sites of the drug’s therapeutic actions are in the liver, bile, and gut lumen.

Beyond conjugation, ursodiol is not altered or catabolized appreciably by the liver or intestinal mucosa. A small proportion of orally administered drug undergoes bacterial degradation with each cycle of enterohepatic circulation. Ursodiol can be both oxidized and reduced at the 7-carbon, yielding either 7-keto-lithocholic acid or lithocholic acid, respectively. Further, there is some bacterially catalyzed deconjugation of glyco- and tauro- ursodeoxycholic acid in the small bowel. Free ursodiol, 7-keto-lithocholic acid, and lithocholic acid are relatively insoluble in aqueous media and larger proportions of these compounds are lost from the distal gut into the feces. Reabsorbed free ursodiol is reconjugated by the liver. Eighty percent of lithocholic acid formed in the small bowel is excreted in the feces, but the 20% that is absorbed is sulfated at the 3-hydroxyl group in the liver to relatively insoluble lithocholyl conjugates which are excreted into bile and lost in feces. Absorbed 7-keto-lithocholic acid is stereospecifically reduced in the liver to chenodiol.

Lithocholic acid causes cholestatic liver injury and can cause death from liver failure in certain species unable to form sulfate conjugates. Lithocholic acid is formed by 7-dehydroxylation of the dihydroxy bile acids (ursodiol and chenodiol) in the gut lumen. The 7-dehydroxylation reaction appears to be alpha-specific, i.e. chenodiol is more efficiently 7-dehydroxylated than ursodiol and, for equimolar doses of ursodiol and chenodiol, levels of lithocholic acid appearing in bile are lower with the former. Man has the capacity to sulfate lithocholic acid. Although liver injury has not been associated with ursodiol therapy, a reduced capacity to sulfate may exist in some individuals, but such a deficiency has not yet been clearly demonstrated.

Pharmacodynamics

Ursodiol suppresses hepatic synthesis and secretion of cholesterol, and also inhibits intestinal absorption of cholesterol. It appears to have little inhibitory effect on synthesis and secretion into bile of endogenous bile acids, and does not appear to affect secretion of phospholipids into bile.

With repeated dosing, bile ursodeoxycholic acid concentrations reach a steady-state in about 3 weeks. Although insoluble in aqueous media, cholesterol can be solubilized in at least two different ways in the presence of dihydroxy bile acids. In addition to solubilizing cholesterol in micelles, ursodiol acts by an apparently unique mechanism to cause dispersion of cholesterol as liquid crystals in aqueous media. Thus, even though administration of high doses (e.g., 15 mg/kg/day to 18 mg/kg/day) does not result in a concentration of ursodiol higher than 60% of the total bile acid pool, ursodiol-rich bile effectively solubilizes cholesterol. The overall effect of ursodiol is to increase the concentration level at which saturation of cholesterol occurs.

The various actions of ursodiol combine to change the bile of patients with gallstones from cholesterol-precipitating to cholesterol-solubilizing, thus resulting in bile conducive to cholesterol stone dissolution.

After ursodiol dosing is stopped, the concentration of the bile acid in bile falls exponentially, declining to about 5% to 10% of its steady-state level in about 1 week.

Clinical Results

Gallstone Dissolution

On the basis of clinical trial results in a total of 868 patients with radiolucent gallstones treated in 8 studies (three in the U.S. involving 282 patients, one in the U.K. involving 130 patients, and four in Italy involving 456 patients) for periods ranging from 6 to 78 months with ursodiol doses ranging from about 5 mg/kg/day to 20 mg/kg/day, an ursodiol dose of about 8 mg/kg/day to 10 mg/kg/day appeared to be the best dose. With an ursodiol dose of about 10 mg/kg/day, complete stone dissolution can be anticipated in about 30% of unselected patients with uncalcified gallstones < 20 mm in maximal diameter treated for up to 2 years. Patients with calcified gallstones prior to treatment, or patients who develop stone calcification or gallbladder non-visualization on treatment, and patients with stones > 20 mm in maximal diameter rarely dissolve their stones. The chance of gallstone dissolution is increased up to 50% in patients with floating or floatable stones (i.e. those with high cholesterol content), and is inversely related to stone size for those < 20 mm in maximal diameter. Complete dissolution was observed in 81% of patients with stones up to 5 mm in diameter. Age, sex, weight, degree of obesity, and serum cholesterol level are not related to the chance of stone dissolution with ursodiol.

A nonvisualizing gallbladder by oral cholecystogram prior to the initiation of therapy is not a contraindication to ursodiol therapy (the group of patients with non-visualizing gallbladders in the ursodiol studies had complete stone dissolution rates similar to the group of patients with visualizing gallbladders). However, gallbladder non-visualization developing during ursodiol treatment predicts failure of complete stone dissolution and in such cases therapy should be discontinued.

Partial stone dissolution occurring within 6 months of beginning therapy with ursodiol appears to be associated with a > 70% chance of eventual complete stone dissolution with further treatment; partial dissolution observed within 1 year of starting therapy indicates a 40% probability of complete dissolution.

Stone recurrence after dissolution with ursodiol therapy was seen within 2 years in 8/27 (30%) of patients in the U.K. studies. Of 16 patients in the U.K. study whose stones had previously dissolved on chenodiol but later recurred, 11 had complete dissolution on ursodiol. Stone recurrence has been observed in up to 50% of patients within 5 years of complete stone dissolution on ursodiol therapy. Serial ultrasonographic examinations should be obtained to monitor for recurrence of stones, bearing in mind that radiolucency of the stones should be established before another course of ursodiol is instituted. A prophylactic dose of ursodiol has not been established.

Gallstone Prevention

Two placebo-controlled, multicenter, double-blind, randomized, parallel group trials in a total of 1,316 obese patients were undertaken to evaluate ursodiol in the prevention of gallstone formation in obese patients undergoing rapid weight loss. The first trial consisted of 1,004 obese patients with a body mass index (BMI) ≥ 38 who underwent weight loss induced by means of a very low calorie diet for a period of 16 weeks. An intent-to-treat analysis of this trial showed that gallstone formation occurred in 23% of the placebo group, while those patients on 300, 600, or 1,200 mg/day of ursodiol experienced a 6%, 3%, and 2% incidence of gallstone formation, respectively. The mean weight loss for this 16-week trial was 47 lb for the placebo group, and 47, 48, and 50 lb for the 300, 600, and 1,200 mg/day ursodiol groups, respectively.

The second trial consisted of 312 obese patients (BMI ≥ 40) who underwent rapid weight loss through gastric bypass surgery. The trial drug treatment period was for 6 months following this surgery. Results of this trial showed that gallstone formation occurred in 23% of the placebo group, while those patients on 300, 600, or 1,200 mg/day of ursodiol experienced a 9%, 1%, and 5% incidence of gallstone formation, respectively. The mean weight loss for this 6-month trial was 64 lb for the placebo group, and 67, 74, and 72 lb for the 300, 600, and 1,200 mg/day ursodiol groups, respectively.

ALTERNATIVE THERAPIES

Watchful Waiting

Watchful waiting has the advantage that no therapy may ever be required. For patients with silent or minimally symptomatic stones, the rate of development of moderate-to-severe symptoms or gallstone complications is estimated to be between 2% and 6% per year, leading to a cumulative rate of 7% to 27% in 5 years. Presumably the rate is higher for patients already having symptoms.

Cholecystectomy

For patients with symptomatic gallstones, surgery offers the advantage of immediate and permanent stone removal, but carries a high risk in some patients. About 5% of cholecystectomized patients have residual symptoms or retained common duct stones. The spectrum of surgical risk varies as a function of age and the presence of disease other than cholelithiasis.

Mortality Rates for Cholecystectomy in the U.S. (National Halothane Study, JAMA 1966; 197:775-8) 27,600 Cholecystectomies (Smoothed Rates) Deaths/1000 Operations***

 | Age (Yrs) | Cholecystectomy | Cholecystectomy + Common Duct Exploration
Low Risk Patients*
Women | 0 to 49; 50 to 69 | 0.54; 2.80 | 2.13; 10.10
Men | 0 to 49; 50 to 69 | 1.04; 5.41 | 4.12; 19.23
High Risk Patients**
Women | 0 to 49; 50 to 69 | 12.66; 17.24 | 47.62; 58.82
Men | 0 to 49; 50 to 69 | 24.39; 33.33 | 90.91; 111.11
* In good health or with moderate systemic disease.
** With severe or extreme systemic disease.
*** Includes both elective and emergency surgery.

Women in good health or who have only moderate systemic disease and are under 49 years of age have the lowest surgical mortality rate (0.054); men in all categories have a surgical mortality rate twice that of women. Common duct exploration quadruples the rates in all categories. The rates rise with each decade of life and increase tenfold or more in all categories with severe or extreme systemic disease.

INDICATIONS AND USAGE

1. Ursodiol capsules are indicated for patients with radiolucent, noncalcified gallbladder stones < 20 mm in greatest diameter in whom elective cholecystectomy would be undertaken except for the presence of increased surgical risk due to systemic disease, advanced age, idiosyncratic reaction to general anesthesia, or for those patients who refuse surgery. Safety of use of ursodiol capsules beyond 24 months is not established.
2. Ursodiol capsules are indicated for the prevention of gallstone formation in obese patients experiencing rapid weight loss.

CONTRAINDICATIONS

1. Ursodiol will not dissolve calcified cholesterol stones, radiopaque stones, or radiolucent bile pigment stones. Hence, patients with such stones are not candidates for ursodiol therapy.
2. Patients with compelling reasons for cholecystectomy including unremitting acute cholecystitis, cholangitis, biliary obstruction, gallstone pancreatitis, or biliary-gastrointestinal fistula are not candidates for ursodiol therapy.
3. Allergy to bile acids.

PRECAUTIONS

Liver Tests

Ursodiol therapy has not been associated with liver damage. Lithocholic acid, a naturally occurring bile acid, is known to be a liver-toxic metabolite. This bile acid is formed in the gut from ursodiol less efficiently and in smaller amounts than that seen from chenodiol. Lithocholic acid is detoxified in the liver by sulfation and, although man appears to be an efficient sulfater, it is possible that some patients may have a congenital or acquired deficiency in sulfation, thereby predisposing them to lithocholate-induced liver damage.

Abnormalities in liver enzymes have not been associated with ursodiol therapy and, in fact, ursodiol has been shown to decrease liver enzyme levels in liver disease. However, patients given ursodiol should have SGOT (AST) and SGPT (ALT) measured at the initiation of therapy and thereafter as indicated by the particular clinical circumstances.

Drug Interactions

Bile acid sequestering agents such as cholestyramine and colestipol may interfere with the action of ursodiol by reducing its absorption. Aluminum-based antacids have been shown to adsorb bile acids in vitro and may be expected to interfere with ursodiol in the same manner as the bile acid sequestering agents. Estrogens, oral contraceptives, and clofibrate (and perhaps other lipid-lowering drugs) increase hepatic cholesterol secretion, and encourage cholesterol gallstone formation and hence may counteract the effectiveness of ursodiol.

Carcinogenesis, Mutagenesis, Impairment of Fertility

Ursodeoxycholic acid was tested in 2-year oral carcinogenicity studies in CD-1 mice and Sprague-Dawley rats at daily doses of 50, 250, and 1,000 mg/kg/day. It was not tumorigenic in mice. In the rat study, it produced statistically significant dose-related increased incidences of pheochromocytomas of adrenal medulla in males (p = 0.014, Peto trend test) and females (p = 0.004, Peto trend test). A 78-week rat study employing intrarectal instillation of lithocholic acid and tauro‑deoxycholic acid, metabolites of ursodiol and chenodiol, has been conducted.

These bile acids alone did not produce any tumors. A tumor-promoting effect of both metabolites was observed when they were co-administered with a carcinogenic agent. Results of epidemiologic studies suggest that bile acids might be involved in the pathogenesis of human colon cancer in patients who had undergone a cholecystectomy, but direct evidence is lacking. Ursodiol is not mutagenic in the Ames test. Dietary administration of lithocholic acid to chickens is reported to cause hepatic adenomatous hyperplasia.

Teratogenic Effects: Pregnancy Category B

Reproduction studies have been performed in rats and rabbits with ursodiol doses up to 200-fold the therapeutic dose and have revealed no evidence of impaired fertility or harm to the fetus at doses of 20- to 100-fold the human dose in rats and at 5-fold the human dose (highest dose tested) in rabbits. Studies employing 100- to 200-fold the human dose in rats have shown some reduction in fertility rate and litter size. There have been no adequate and well-controlled studies of the use of ursodiol in pregnant women, but inadvertent exposure of 4 women to therapeutic doses of the drug in the first trimester of pregnancy during the ursodiol trials led to no evidence of effects on the fetus or newborn baby. Although it seems unlikely, the possibility that ursodiol can cause fetal harm cannot be ruled out; hence, the drug is not recommended for use during pregnancy.

Nursing Mothers

It is not known whether ursodiol is excreted in human milk. Because many drugs are excreted in human milk, caution should be exercised when ursodiol is administered to a nursing mother.

Pediatric Use

The safety and effectiveness of ursodiol in pediatric patients have not been established.

Geriatric Use

In worldwide clinical studies of ursodiol, approximately 14% of subjects were over 65 years of age (approximately 3% were over 75 years old). In a subgroup analysis of existing clinical trials, patients greater than 56 years of age did not exhibit statistically significantly different complete dissolution rates from the younger population. No age-related differences in safety and effectiveness were found. Other reported clinical experience has not identified differences in response in elderly and younger patients. However, small differences in efficacy and greater sensitivity of some elderly individuals taking ursodiol cannot be ruled out. Therefore, it is recommended that dosing proceed with caution in this population.

ADVERSE REACTIONS

The nature and frequency of adverse experiences were similar across all groups.

The following tables provide comprehensive listings of the adverse experiences reported that occurred with a 5% incidence level:

GALLSTONE DISSOLUTION

 | Ursodiol; 8 mg/kg/day to 10 mg/kg/day; (N = 155) |  | Placebo; (N = 159)
 | N | (%) | N | (%)
Body as a Whole
Allergy; Chest Pain; Fatigue; Infection Viral | 8; 5; 7; 30 | (5.2); (3.2); (4.5); (19.4) | 7; 10; 8; 41 | (4.4); (6.3); (5.0); (25.8)
Digestive System
Abdominal Pain; Cholecystitis; Constipation; Diarrhea; Dyspepsia; Flatulence; Gastrointestinal Disorder; Nausea; Vomiting | 67; 8; 15; 42; 26; 12; 6; 22; 15 | (43.2); (5.2); (9.7); (27.1); (16.8); (7.7); (3.9); (14.2); (9.7) | 70; 7; 14; 34; 18; 12; 8; 27; 11 | (44.0); (4.4); (8.8); (21.4); (11.3); (7.5); (5.0); (17.0); (6.9)
Musculoskeletal System
Arthralgia; Arthritis; Back Pain; Myalgia | 12; 9; 11; 9 | (7.7); (5.8); (7.1); (5.8) | 24; 4; 18; 9 | (15.1); (2.5); (11.3); (5.7)
Nervous System
Headache; Insomnia | 28; 3 | (18.1); (1.9) | 34; 8 | (21.4); (5.0)
Respiratory System
Bronchitis; Coughing; Pharyngitis; Rhinitis; Sinusitis; Upper Respiratory Tract Infection | 10; 11; 13; 8; 17; 24 | (6.5); (7.1); (8.4); (5.2); (11.0); (15.5) | 6; 7; 5; 11; 18; 21 | (3.8); (4.4); (3.1); (6.9); (11.3); (13.2)
Urogenital System
Urinary Tract Infection | 10 | (6.5) | 7 | (4.4)

GALLSTONE PREVENTION

 | Ursodiol,; 600 mg; (N = 322) |  | Placebo; (N = 325)
 | N | (%) | N | (%)
Body as a Whole
Fatigue; Infection Viral; Influenza-like Symptoms | 25; 29; 21 | (7.8); (9.0); (6.5) | 33; 29; 19 | (10.2); (8.9); (5.8)
Digestive System
Abdominal Pain; Constipation; Diarrhea; Flatulence; Nausea; Vomiting | 20; 85; 81; 15; 56; 44 | (6.2); (26.4); (25.2); (4.7); (17.4); (13.7) | 39; 72; 68; 24; 43; 44 | (12.0); (22.2); (20.9); (7.4); (13.2); (13.5)
Musculoskeletal System
Back Pain; Musculoskeletal Pain | 38; 19 | (11.8); (5.9) | 21; 15 | (6.5); (4.6)
Nervous System
Dizziness; Headache | 53; 80 | (16.5); (24.8) | 42; 78 | (12.9); (24.0)
Respiratory System
Pharyngitis; Sinusitis; Upper Respiratory Tract Infection | 10; 17; 40 | (3.1); (5.3); (12.4) | 19; 18; 35 | (5.8); (5.5); (10.8)
Skin and Appendages
Alopecia | 17 | (5.3) | 8 | (2.5)
Urogenital System
Dysmenorrhea | 18 | (5.6) | 19 | (5.8)

To report SUSPECTED ADVERSE REACTIONS, contact AvKARE at 1-855-361-3993 or FDA at 1-800-FDA-1088 or www.fda.gov/medwatch.

OVERDOSAGE

Neither accidental nor intentional overdosing with ursodioll has been reported. Doses of ursodiol in the range of 16 to 20 mg/kg/day have been tolerated for 6 to 37 months without symptoms by 7 patients. The LD50 for ursodiol in rats is over 5,000 mg/kg given over 7 to 10 days and over 7,500 mg/kg for mice. The most likely manifestation of severe overdose with ursodiol would probably be diarrhea, which should be treated symptomatically.

DOSAGE AND ADMINISTRATION

Gallstone Dissolution

The recommended dose for ursodiol capsules treatment of radiolucent gallbladder stones is 8 to 10 mg/kg/day given in 2 or 3 divided doses.

Ultrasound images of the gallbladder should be obtained at 6-month intervals for the first year of ursodiol capsules therapy to monitor gallstone response. If gallstones appear to have dissolved, ursodiol capsules therapy should be continued and dissolution confirmed on a repeat ultrasound examination within 1 to 3 months. Most patients who eventually achieve complete stone dissolution will show partial or complete dissolution at the first on-treatment reevaluation. If partial stone dissolution is not seen by 12 months of ursodiol capsules therapy, the likelihood of success is greatly reduced.

Gallstone Prevention

The recommended dosage of ursodiol capsules for gallstone prevention in patients undergoing rapid weight loss is 600 mg/day (300 mg b.i.d.).

HOW SUPPLIED

Ursodiol Capsules USP, 300 mg are supplied as opaque white body and pink cap, imprinted “AN” on one half and “1540” on the other half of the capsules in black.

They are available as follows:

NDC 50268-797-15 (10 capsules per card, 5 cards per carton).

Store at 20° to 25°C (68° to 77°F) [see USP Controlled Room Temperature].

For Institutional Use Only. Dispensed in Unit Dose Package.

Keep this and all medications out of reach of children.

Manufactured for:

AvKARE

Pulaski, TN 38478

Mfg. Rev. 12-2017-00

AV 02/21 (P)

AvPAK